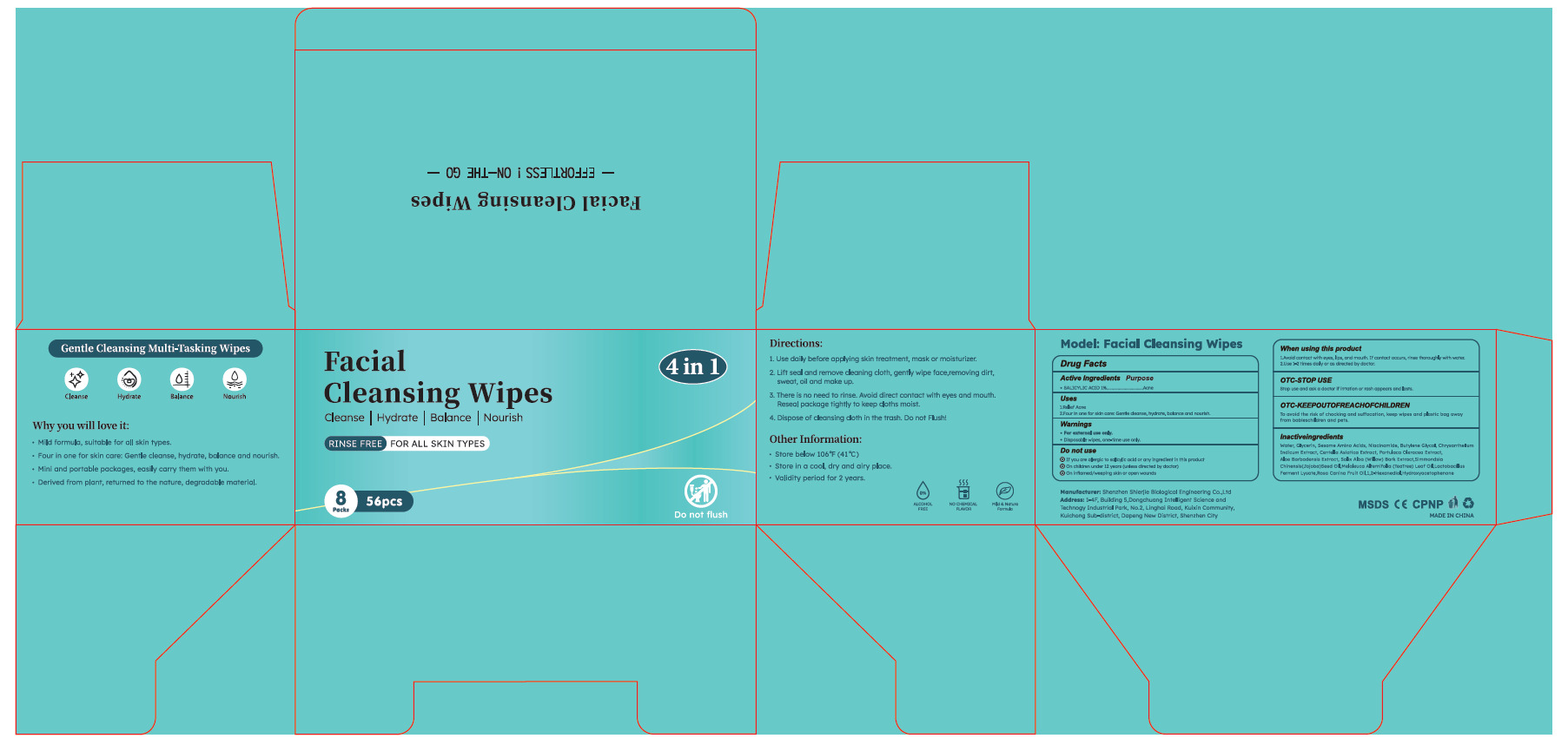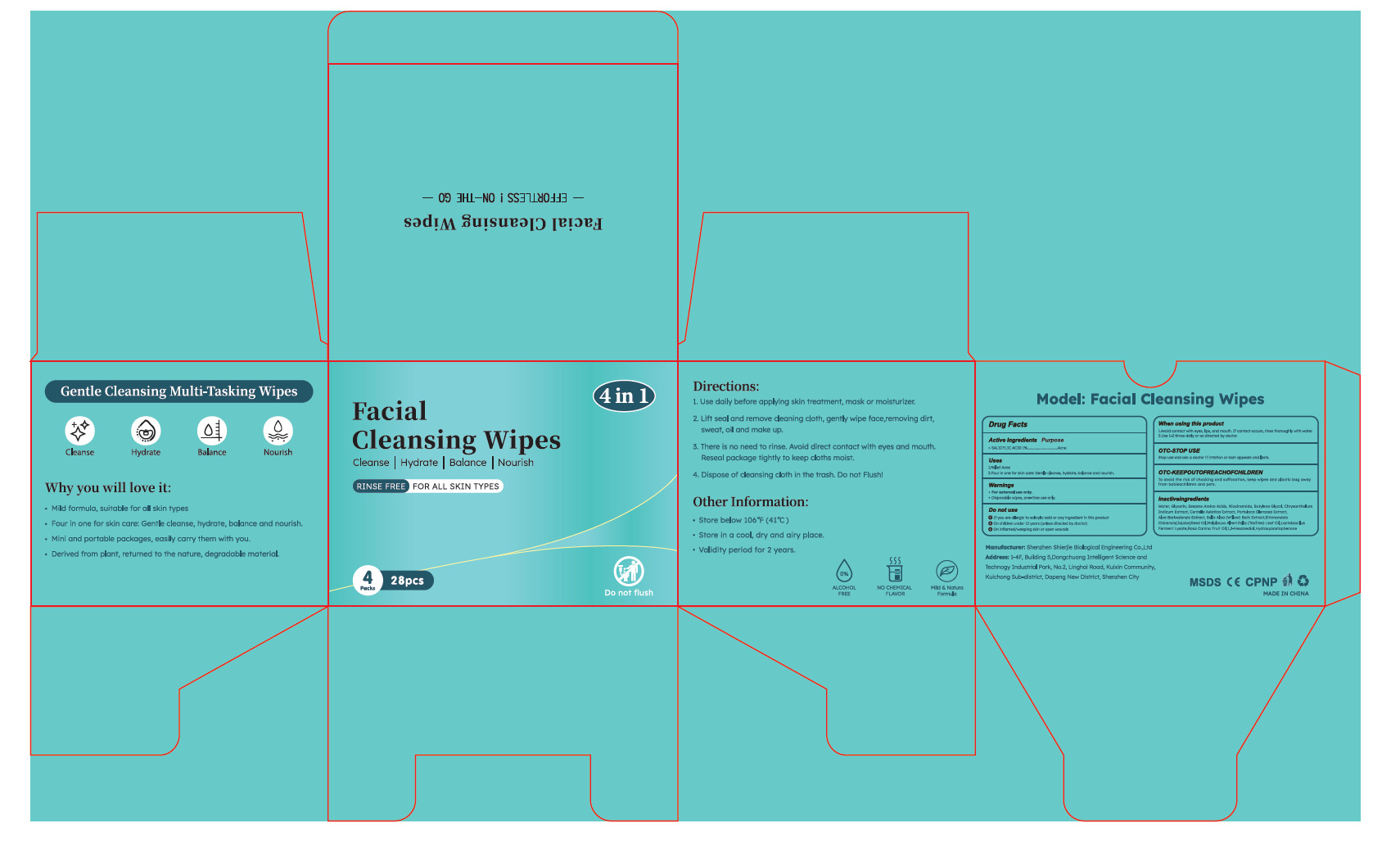 DRUG LABEL: Facial Cleansing Wipes
NDC: 43116-041 | Form: CLOTH
Manufacturer: Shenzhen Shierjie Biological Engineering Co., LTD
Category: otc | Type: HUMAN OTC DRUG LABEL
Date: 20250607

ACTIVE INGREDIENTS: SALICYLIC ACID 1 U/100 U
INACTIVE INGREDIENTS: HYDROXYACETOPHENONE; SALIX ALBA BARK; MELALEUCA ALTERNIFOLIA (TEA TREE) LEAF OIL; ROSA CANINA FRUIT OIL; WATER; GLYCERIN; SESAME SEED; NIACINAMIDE; BUTYLENE GLYCOL; CHRYSANTHELLUM INDICUM TOP; CENTELLA ASIATICA TRITERPENOIDS; PURSLANE; SIMMONDSIA CHINENSIS (JOJOBA) SEED OIL; ALOE BARBADENSIS LEAF; LIMOSILACTOBACILLUS FERMENTUM; 1,2-HEXANEDIOL

43116-041

Active Ingredient

SAL ICYLIC ACID 1%

Purpose

Acne

Use

1.Relief Acne
2.Four in one for skin care: Gentle cleanse, hydrate, balance and nourish.

Warnings

●For external use only.
●Disposable wipes, one-time use only.

Do not use

1. If you are allergic to salicylic acid or any ingredient in this product
2. On children under 12 years (unless directed by doctor)
3. On inflamed/weeping skin or open wounds

When Using

1.Avoid contact with eyes, lips, and mouth. If contact occurs, rinse thoroughly with water.
2.Use 1-2 times daily or as directed by doctor.

Stop Use

Stop use and ask a doctor if irtation or rash appears and lasts.

Keep Oot Of Reach Of Children

To avid the isk of chocking and ufocationnn keep wipes and plastic bag awoy
from babieschildren and pets.

Directions

1. Use daily before applying skin treatment, mask or moisturizer.
2. Lift seal and remove cleaning cloth, gently wipe face,removing dirt, sweat, oil and make up.
3. There is no need to rinse. Avoid direct contact with eyes and mouth. Reseal package tightly to keep cloths moist.
4. Dispose of cleansing cloth in the trash. Do not Flush!

Other information

●Store below 106°F (41°C)
●Store in a cool, dry and airy place.
●Validity period for 2 years.

Inactive ingredients

Water, Glycerin, Sesame Amino Acids, Niacinamide, Butylene Glycol, Chrysanthellum
Indicum Extract, Centella Asiatica Extract, Portulaca Oleracea Extract,
Aloe Barbadensis Extract, Salix Alba (Willow) Bark Extract Simmondsia
Chinensis(Jojoba)Seed Oil,Melaleuca Alternifolia (TeaTree) Leaf Oil,Lactobacillus
Ferment Lysate,Rosa Canina Fruit Oil,1,2-Hexanediol,Hydroxyacetophenone